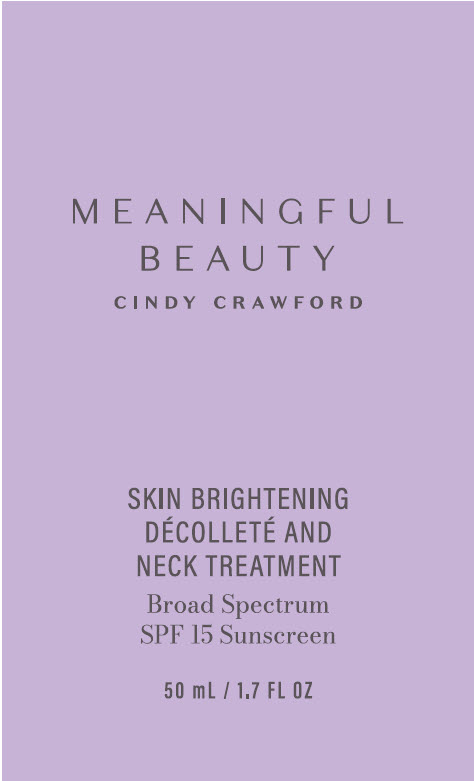 DRUG LABEL: Meaningful Beauty Cindy Crawford Skin Brightening Decollete and Neck Treatment Broad Spectrum SPF 15
NDC: 84068-002 | Form: CREAM
Manufacturer: Meaningful Beauty, LLC
Category: otc | Type: HUMAN OTC DRUG LABEL
Date: 20250512

ACTIVE INGREDIENTS: Avobenzone 3 mg/100 mL; Octinoxate 7.5 mg/100 mL; Octisalate 5 mg/100 mL; Oxybenzone 5 mg/100 mL
INACTIVE INGREDIENTS: water; Neopentyl Glycol Diheptanoate; Dicaprylyl Carbonate; CETOSTEARYL ALCOHOL; Butylene Glycol; Glycerin; PEG-40 MONOSTEARATE; PEG-100 MONOSTEARATE; GLYCERYL MONOSTEARATE; Dimethicone; MUSKMELON; ARCTOSTAPHYLOS UVA-URSI LEAF; Ascorbyl Methylsilanol Pectinate; Magnesium Ascorbyl Phosphate; Tetrapeptide-21; Biosaccharide Gum-1; GLYCYRRHIZINATE DIPOTASSIUM; Caprylyl Glycol; HYDROGENATED PALM OIL; Alcohol; HYDROGENATED SOYBEAN LECITHIN; SOYBEAN PHOSPHATIDYLCHOLINE; Cholesterol; Ethylhexylglycerin; Polysorbate 60; HYDROXYETHYL ACRYLATE/SODIUM ACRYLOYLDIMETHYL TAURATE COPOLYMER (100000 MPA.S AT 1.5%); Steareth-20; EDETATE DISODIUM; Potassium Sorbate; Sodium Hydroxide; Chlorphenesin; Phenoxyethanol

Meaningful Beauty Cindy Crawford Skin Brightening Décolleté and Neck Treatment Broad Spectrum SPF 15

Drug Facts

Active ingredients

Avobenzone 3.0%, Octinoxate 7.5%, Octisalate 5.0%, Oxybenzone 5.0%

Purpose

Sunscreen

Uses

- Helps prevent sunburn

Warnings

For external use only.

Do not use on damaged or broken skin.

When using this product keep out of eyes. Rinse with water to remove.

Stop use and ask a doctor if rash occurs.

Keep out of reach of children. If product is swallowed, get medical help or contact a Poison Control Center right away.

Directions

- apply generously 15 minutes before sun exposure
- reapply at least every 2 hours
- children under 6 months of age: Ask a doctor
- Sun Protection Measures: Spending time in the sun increases your risk of skin cancer and early skin aging. To decrease this risk, regularly use a sunscreen with a broad spectrum SPF value of 15 or higher and other sun protection measures including:
  - limit time in the sun, especially from 10 a.m.-2 p.m.
  - wear long-sleeve shirts, pants, hats, and sunglasses
  - use a water resistant sunscreen if swimming or sweating

Other Information

- protect this product from excessive heat and direct sun

Inactive ingredients

Water, Neopentyl Glycol Diheptanoate, Dicaprylyl Carbonate, Cetearyl Alcohol, Butylene Glycol, Glycerin, PEG-40 Stearate, PEG-100 Stearate, Glyceryl Stearate, Dimethicone, Cucumis Melo (Melon) Fruit Extract, Arctostaphylos Uva Ursi Leaf Extract, Ascorbyl Methylsilanol Pectinate, Magnesium Ascorbyl Phosphate, Tetrapeptide-21, Biosaccharide Gum-1, Dipotassium Glycyrrhizate, Caprylyl Glycol, Hydrogenated Vegetable Oil, Alcohol, Hydrogenated Lecithin, Hydrogenated Phosphatidylcholine, Cholesterol, Ethylhexylglycerin, Polysorbate 60, Hydroxyethyl Acrylate/Sodium Acryloyldimethyl Taurate Copolymer, Steareth-20, Disodium EDTA, Potassium Sorbate, Sodium Hydroxide, Chlorphenesin, Phenoxyethanol, Fragrance

Questions or Comments?

Within US 1-800-927-0047

PRINCIPAL DISPLAY PANEL - 50 mL Tube Label

MEANINGFUL
BEAUTY
CINDY CRAWFORD

SKIN BRIGHTENING
DÉCOLLETÉ AND
NECK TREATMENT

Broad Spectrum
SPF 15 Sunscreen

50 mL / 1.7 FL OZ